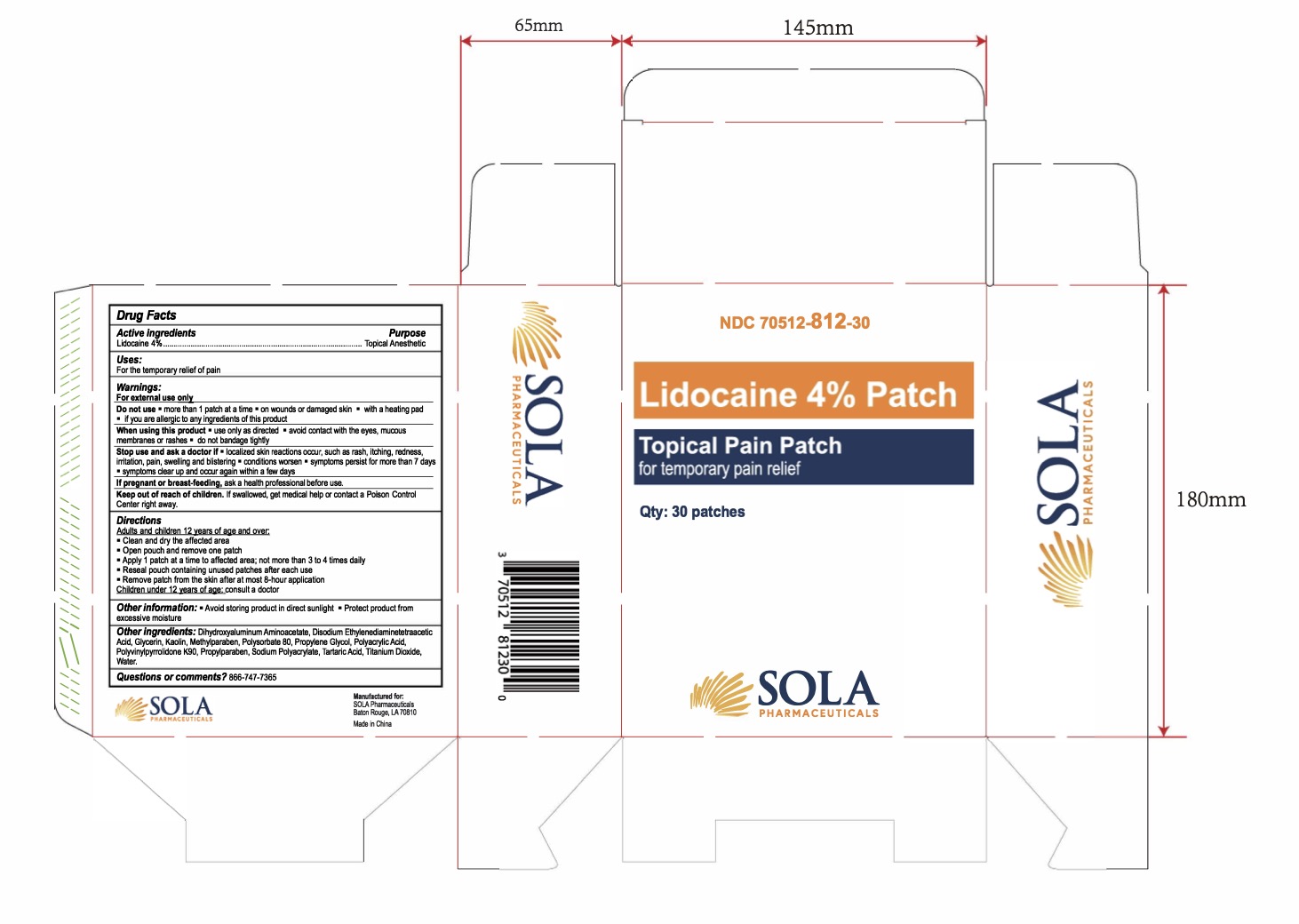 DRUG LABEL: Lidocaine 4% Patch
NDC: 70512-812 | Form: PATCH
Manufacturer: SOLA Pharmaceuticals
Category: otc | Type: HUMAN OTC DRUG LABEL
Date: 20251208

ACTIVE INGREDIENTS: LIDOCAINE 40 mg/1 g
INACTIVE INGREDIENTS: TITANIUM DIOXIDE; GLYCERIN; DISODIUM ETHYLENEDIAMINEDIACETATE; SODIUM POLYACRYLATE (2500000 MW); PROPYLPARABEN; WATER; KAOLIN; POLYSORBATE 80; POVIDONE K90; DIHYDROXYALUMINUM AMINOACETATE; PROPYLENE GLYCOL; POLYACRYLIC ACID (250000 MW); TARTARIC ACID

Lidocaine 4% Patch

Active Ingredients

Lidocaine

Purpose

Topical Anesthetic

Uses

For the temporary relief of pain

Warnings

For external use only

Do not use

- more than 1 patch at a time
- on wounds or damaged skin
- with a heating pad
- if you are allergic to any ingredients of this product

When using this product

- use only as directed
- avoid contact with the eyes, mucous membranes or rashes
- do not bandage tightly

Stop use and ask a doctor if

- localized skin reactions occur, such as rash, itching, redness, irritation, pain, swelling and blistering
- conditions worsen
- symptoms persist for more than 7 days
- symptoms clear up and occur again within a few days

PREGNANCY OR BREAST FEEDING

If pregnant or breast-feeding, ask a health care professional before use.

Keep out of reach of children. If swallowed, get medical help or contact a Poison Control Center right away.

Directions

Adults and children 12 years of age and over:

- Clean and dry the affected area
- Open pouch and remove one patch
- Apply 1 patch at a time to affected area; not more than 3 to 4 times daily
- Reseal pouch containing unused patches after each use
- Remove patch from the skin after at most 8-hour application

Children under 12 years of age: consult a doctor

Other Information

- Avoid storing product in direct sunlight
- Protect product from excessive moisture

Other Ingredients

Dihydroxyaluminum Aminoacetate, Disodium Ethylenediaminetetraacetic Acid, Glycerin, Kaolin, Methylparaben, Polysorbate 80, Propylene Glycol, Polyacrylic Acid, Polyvinylpyrrolidone K90, Propylparaben, Sodium Polyacrylate, Tartaric Acid, Titanium Dioxide, Water.

Questions or comments? 866-747-7365

Lidocaine 4% Patch

NDC 70512-812-30

Qty: 30 patches

Manufactured for:

SOLA Pharmaceuticals

Baton Rouge, LA 70810

Made in China